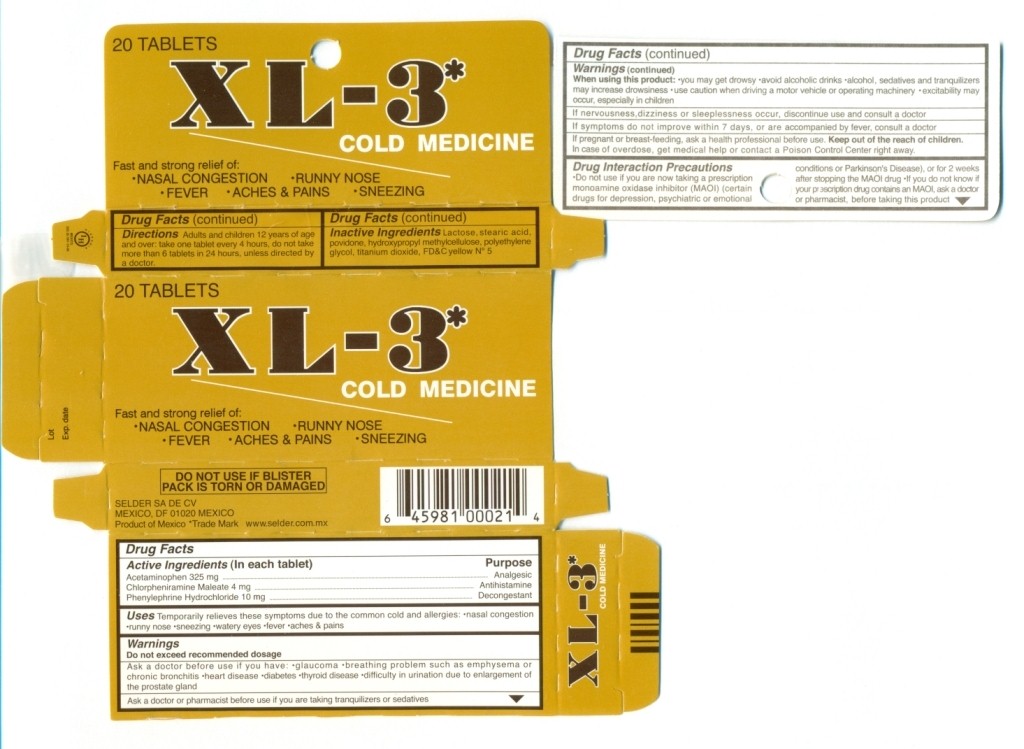 DRUG LABEL: Cold Medicine
NDC: 63654-600 | Form: TABLET
Manufacturer: Selder, S.A. de C.V.
Category: otc | Type: HUMAN OTC DRUG LABEL
Date: 20111020

ACTIVE INGREDIENTS: ACETAMINOPHEN 325 mg/1 1; CHLORPHENIRAMINE MALEATE 4 mg/1 1; PHENYLEPHRINE HYDROCHLORIDE 10 mg/1 1
INACTIVE INGREDIENTS: LACTOSE; STEARIC ACID; POVIDONE; HYPROMELLOSES; POLYETHYLENE GLYCOLS; TITANIUM DIOXIDE; FD&C YELLOW NO. 5

Drug Facts

Active Ingredients (in each capsule)
Acetaminophen 325 mg
Chlorpheniramine Maleate 4 mg
Phenylepherine Hydrochloride 10 mg

Purpose
Analgesic
Antihistamine
Decongestant

INDICATIONS AND USAGE

Uses temporarily relieves these symptoms due to common cold and allergies: • nasal congestion • runny nose • sneezing • watery eyes • fever • aches and pains

Warnings
Do exceedrecommended dosage

Ask a doctor before use you have
• glaucoma • breathing problem such as emphysema or chronic bronchitis • heart disease • diabetes • thyroid disease
• difficulty in urination due to enlargement of the prostate gland

Ask a doctor or pharmacist before use if you are taking tranquilizers or sedatives

STOP USE

Stop taking this product and ask a doctor if you have • pain • fever or symptoms that persist or get worse • new symptoms occur
• redness or swelling • these may be signs of a serious condition.

When using this product
• you may get drowsy • avoid alcoholic drinks
• alcohol, sedatives and tranquilizers may increase drowsiness
• use caution when driving a motor vehicle or operating machinery
• excitability may occur, especially in children
If nervousness, dizziness or sleeplessness occur discontinue use and consult a doctor
If symptoms do not improve within 7 days, or are accompanied by fever, consult a doctor
If pregnant or breast feeding, ask a health professional before use

KEEP OUT OF REACH OF CHILDREN

Keep this and all drugs out of the reach of children. In case of accidental overdose, get medical help or contact a Poison Control Center immediately.

Drug Interaction Precautions
• Do not use if you are taking a prescription monoamine oxidase inhibitor (MAOI) (certain drugs for depression, psychiatric or emotional conditions, or
Parkinson’s disease), or for 2 weeks after stopping the MAOI drug. • If you do not know if your prescription drug contains an MAOI, ask a doctor or pharmacist before taking this product.

DOSAGE AND ADMINISTRATION

Directions Adults and children 12 years of age and older; take 1 tablet every 4 hours, do not take more than 6 tablets in 24 hours, unless directed by a doctor.

INACTIVE INGREDIENT

Inactive Ingredients Lactose, stearic acid, povidone, hydroxypropylmethylcellulose, polyethylene glycol, titanium dioxide, FDC Yellow No. 5

Package Label